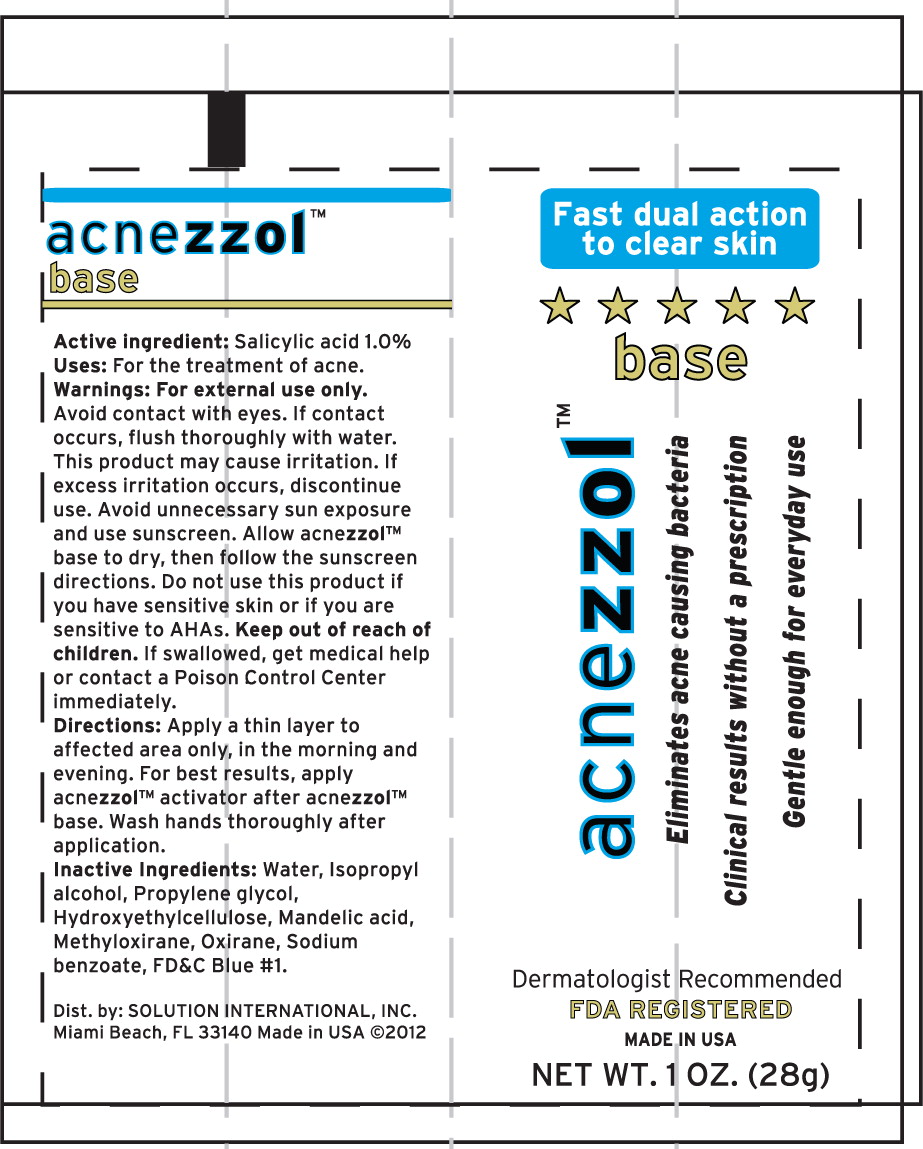 DRUG LABEL: Acnezzol Base
NDC: 58268-013 | Form: LOTION
Manufacturer: SOLUTION INTERNATIONAL INC
Category: otc | Type: HUMAN OTC DRUG LABEL
Date: 20130418

ACTIVE INGREDIENTS: Salicylic Acid 1.0 mg/1 mL
INACTIVE INGREDIENTS: Water; Isopropyl Alcohol; Propylene Glycol; HYDROXYETHYL CELLULOSE (2000 MPA.S AT 1%); Mandelic Acid; Sodium Benzoate; FD&C BLUE NO. 1; Propylene Oxide

acnezzol™
base

Active ingredient:

Salicylic acid 1.0%

Uses:

For the treatment of acne.

Warnings:

For external use only. Avoid contact with eyes. If contact occurs, flush thoroughly with water. This product may cause irritation. If excess irritation occurs, discontinue use. Avoid unnecessary sun exposure and use sunscreen. Allow acnezzol™ base to dry, then follow the sunscreen directions. Do not use this product if you have sensitive skin or If you are sensitive to AH As.

Keep out of reach of children. If swallowed, get medical help or contact a Poison Control Center immediately.

Directions:

Apply a thin layer to affected area only, In the morning and evening. For best results, apply acnezzol™ activator after acnezzol™ base. Wash hands thoroughly after application.

Inactive Ingredients:

Water, Isopropyl alcohol, Propylene glycol, Hydroxyethylcellulose, Mandelic acid, Methyloxirane, Oxirane, Sodium benzoate, FD&C Blue #1.

Dist. by: SOLUTION INTERNATIONAL, INC.

Miami Beach, FL 33140 Made in USA ©2012

Principal Display Panel – Tube Label

Fast dual action
to clear skin

acnezzol™ base

Eliminates acne causing bacteria

Clinical results without a prescription

Gentle enough for everyday use

Dermatologist Recommended
FDA REGISTERED
MADE IN USA
NET WT. 1 OZ. (28 G)